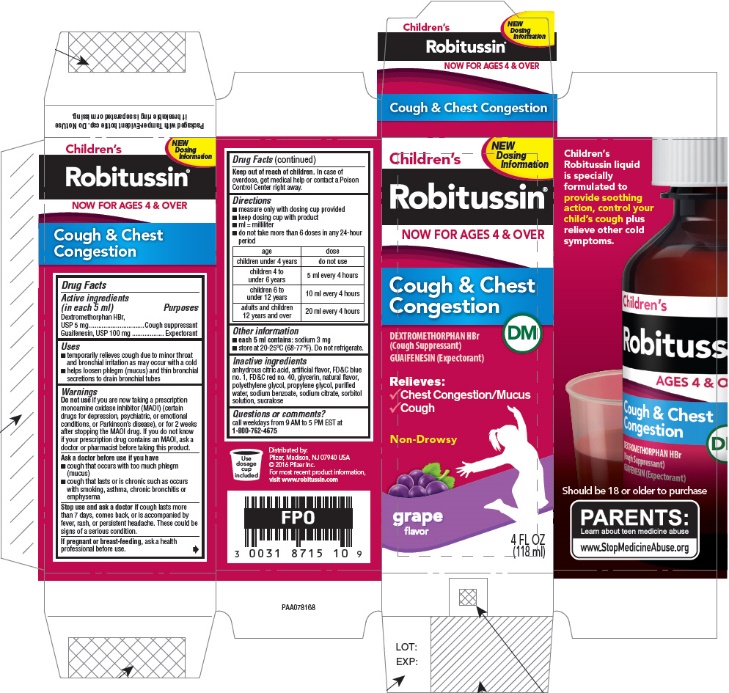 DRUG LABEL: Childrens Robitussin Cough and Chest Congestion DM
NDC: 0031-8715 | Form: LIQUID
Manufacturer: Haleon US Holdings LLC
Category: otc | Type: HUMAN OTC DRUG LABEL
Date: 20240317

ACTIVE INGREDIENTS: DEXTROMETHORPHAN HYDROBROMIDE 5 mg/5 mL; GUAIFENESIN 100 mg/5 mL
INACTIVE INGREDIENTS: ANHYDROUS CITRIC ACID; FD&C BLUE NO. 1; FD&C RED NO. 40; GLYCERIN; POLYETHYLENE GLYCOL, UNSPECIFIED; PROPYLENE GLYCOL, (R)-; WATER; SODIUM BENZOATE; SODIUM CITRATE, UNSPECIFIED FORM; SORBITOL; SUCRALOSE

Drug Facts

Active ingredients (in each 5 ml)

Dextromethorphan HBr, USP 5 mg

Guaifenesin, USP 100 mg

Purposes

Cough suppressant

Expectorant

Uses

- temporarily relieves cough due to minor throat and bronchial irritation as may occur with a cold
- helps loosen phlegm (mucus) and thin bronchial secretions to drain bronchial tubes

Warnings

DO NOT USE

Do not useif you are now taking a prescription monoamine oxidase inhibitor (MAOI) (certain drugs for depression, psychiatric, or emotional conditions, or Parkinson's disease), or for 2 weeks after stopping the MAOI drug. If you do not know if your prescription drug contains an MAOI, ask a doctor or pharmacist before taking this product.

Ask a doctor before use if you have

- cough that occurs with too much phlegm (mucus)
- cough that lasts or is chronic such as occurs with smoking, asthma, chronic bronchitis or emphysema

Stop use and ask a doctor ifcough lasts more than 7 days, comes back, or is accompanied by fever, rash, or persistent headache. These could be signs of a serious condition.

PREGNANCY OR BREAST FEEDING

If pregnant or breast-feeding,ask a health professional before use.

Keep out of reach of children.In case of overdose, get medical help or contact a Poison Control Center right away.

Directions

- measure only with dosing cup provided
- keep dosing cup with product
- ml = milliliter
- do not take more than 6 doses in any 24-hour period

age | dose
children under 4 years | do not use
children 4 to under 6 years | 5 ml every 4 hours
children 6 to under 12 years | 10 ml every 4 hours
adults and children 12 years and over | 20 ml every 4 hours

Other information

- each 5 ml contains:sodium 3 mg
- store at 20-25°C (68-77°F). Do not refrigerate.

Inactive ingredients

anhydrous citric acid, artificial flavor, FD&C blue no. 1, FD&C red no. 40, glycerin, natural flavor, polyethylene glycol, propylene glycol, purified water, sodium benzoate, sodium citrate, sorbitol solution, sucralose

Questions or comments?

call weekdays from 9 AM to 5 PM EST at 1-800-762-4675

For most recent product information, visit www.robitussin.com

Distributed by:
Pfizer, Madison, NJ 07940 USA

PRINCIPAL DISPLAY PANEL

NEW
Dosing
Information

Children's
Robitussin®
NOW FOR AGES 4 & OVER

Cough & Chest
Congestion

DM

DEXTROMETHORPHAN HBr
(Cough Suppressant)
GUAIFENESIN (Expectorant)

Relieves:

✓ Chest Congestion/Mucus
✓ Cough

Non-Drowsy

grape
flavor

4 FL OZ
(118 ml)